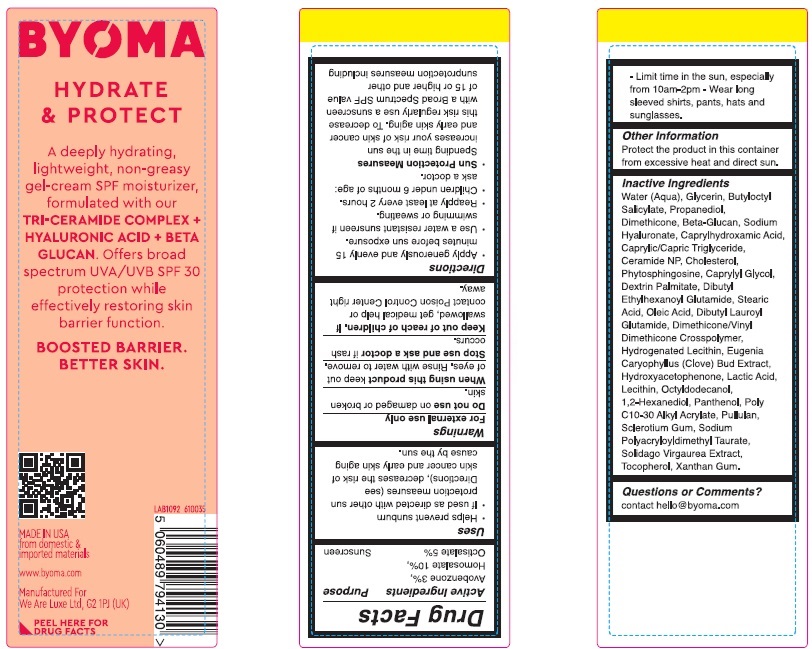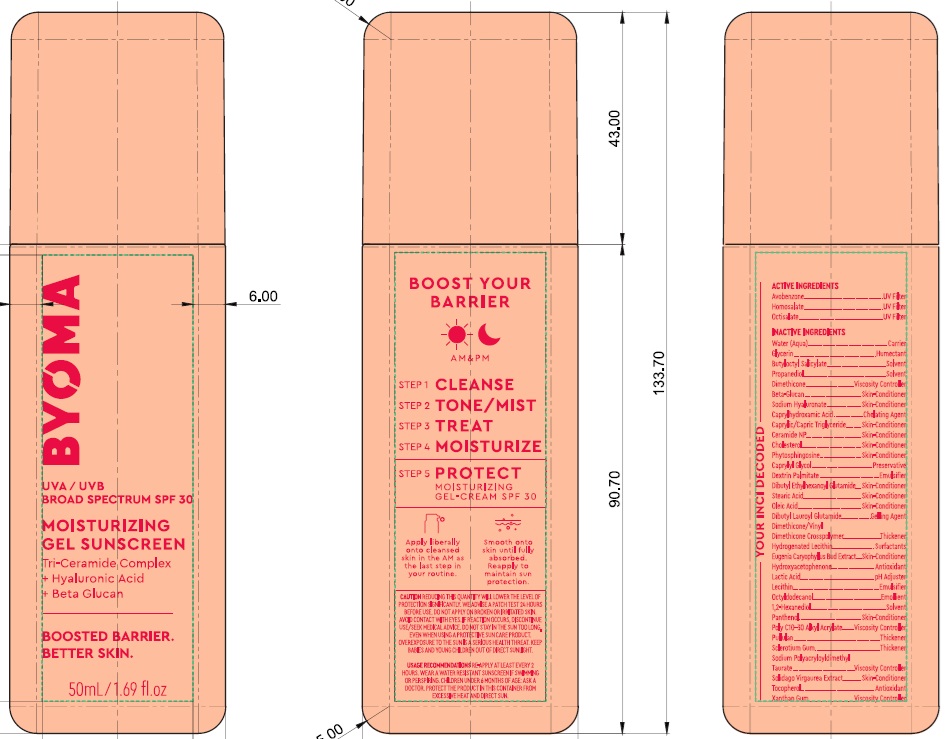 DRUG LABEL: Byoma Moisturizing Sunscreen SPF 30
NDC: 84821-001 | Form: GEL
Manufacturer: BYOMA LIMITED
Category: otc | Type: HUMAN OTC DRUG LABEL
Date: 20241101

ACTIVE INGREDIENTS: AVOBENZONE 30 mg/1 mL; OCTISALATE 50 mg/1 mL; HOMOSALATE 100 mg/1 mL
INACTIVE INGREDIENTS: PHYTOSPHINGOSINE; BEHENYL ACRYLATE POLYMER; SOLIDAGO VIRGAUREA WHOLE; CAPRYLHYDROXAMIC ACID; CERAMIDE NP; DIBUTYL LAUROYL GLUTAMIDE; GLYCERIN; PROPANEDIOL; SODIUM HYALURONATE; DIBUTYL ETHYLHEXANOYL GLUTAMIDE; PANTHENOL; CAPRYLYL GLYCOL; XANTHAN GUM; LECITHIN, SUNFLOWER; DIMETHICONE; YEAST .BETA.-D-GLUCAN; PULLULAN; CAPRYLIC/CAPRIC TRIGLYCERIDE; WATER; BUTYLOCTYL SALICYLATE; HYDROGENATED SOYBEAN LECITHIN; STEARIC ACID; OLEIC ACID; EUGENIA CARYOPHYLLUS (CLOVE) BUD EXTRACT; HYDROXYACETOPHENONE; LACTIC ACID; SCLEROTIUM GUM; DEXTRIN PALMITATE (CORN; 20000 MW); DIMETHICONE/VINYL DIMETHICONE CROSSPOLYMER (SOFT PARTICLE); OCTYLDODECANOL; 1,2-HEXANEDIOL; SODIUM POLYACRYLOYLDIMETHYL TAURATE; TOCOPHEROL; CHOLESTEROL

Byoma Moisturizing Sunscreen SPF 30

Active Ingredients

Avobenzone 3%,

Homosalate 10%,

Octisalate 5%

Purpose

Sunscreen

Uses

- Helps prevent sunburn
- If used as directed wtih other sun protection measures (see Directions), decreases the risk of skin cancer and early skin aging cause by the sun.

Warnings

For external use only

When using this product

keep out of eyes. Rinse with water to remove.

Do not use

on damaged or broken skin.

Stop use and ask a doctor

if rash occurs.

Keep out of reach of children.

If swallowed, get medical help or contact Poison Control Center right away.

Directions

- Apply generously and evenly 15 minutes before sun exposure.
- Use a water resistant sunscreen if swiming or sweating.
- Reapply at least every 2 hours.
- Children under 6 months of age: ask a doctor.
- Sun Protection Measures. Spending time in the sun increases your risk of skin cancer and early skin aging. To decrease this risk regularly use a sunscreen with a Broad Spectrum SPF value of 15 or higher and other sunprotection measures including
- Limit time in the sun, especially from 10am-2pm
- Wear long sleeved shirts, pants, hats and sunglasses.

Other Information

Protect the product in this container from excessive heat and direct sun.

Inactive Ingredients

Water (Aqua), Glycerin, Butyloctyl Salicylate, Propanediol, Dimethicone, Beta-Glucan, Sodium Hyaluronate, Caprylhydroxamic Acid, Caprylic/Capric Triglyceride, Ceramide NP, Cholesterol, Phytosphingosine, Caprylyl Glycol, Dextrin Palmitate, Dibutyl Ethylhexanoyl Glutamide, Stearic Acid, Oleic Acid, Dibutyl Lauroyl Glutamide, Dimethicone/Vinyl Dimethicone Crosspolymer, Hydrogenated Lecithin, Eugenia Caryophyllus (Clove) Bud Extract, Hydroxyacetophenone, Lactic Acid, Lecithin, Octyldodecanol, 1,2-Hexanediol, Panthenol, Poly C10-30 Alkyl Acrylate, Pullulan, Sclerotium Gum, Sodium Polyacryloyldimethyl Taurate, Solidago Virgaurea Extract, Tocopherol, Xanthan Gum.

Questions or Comments?

contact hello@byoma.com